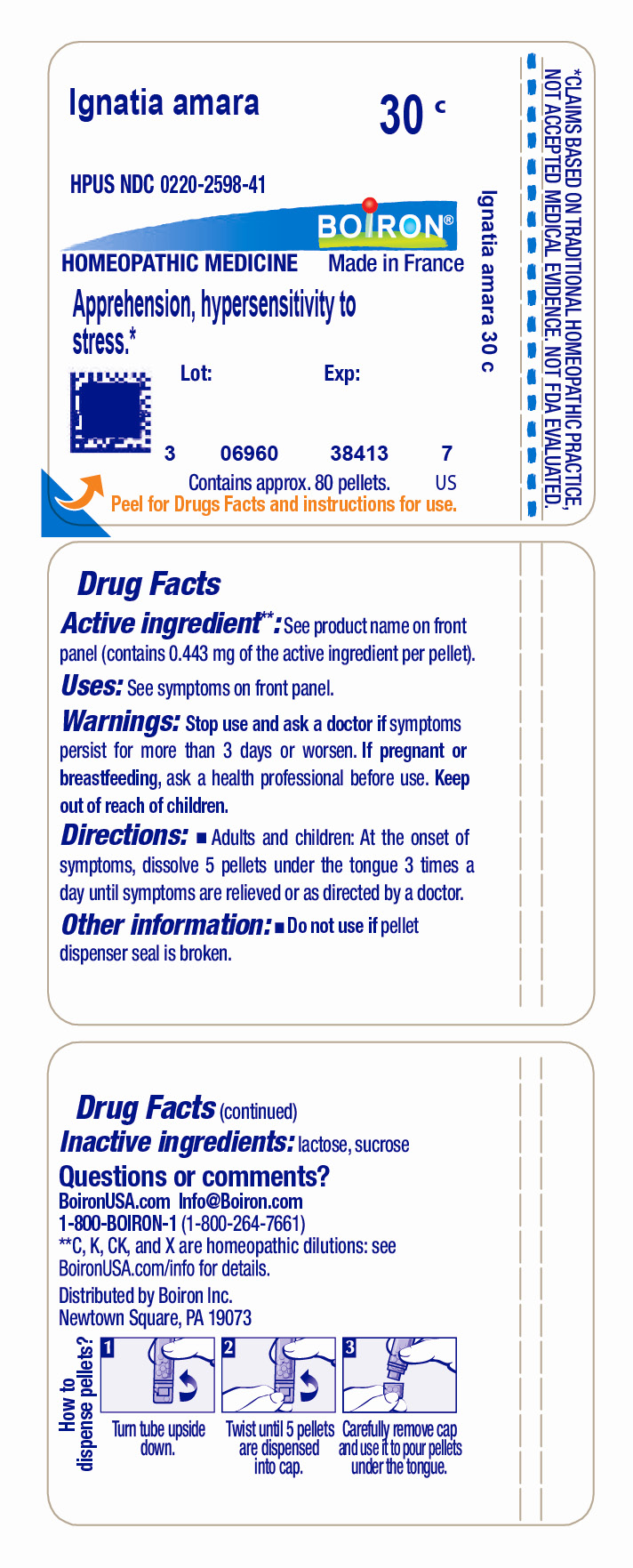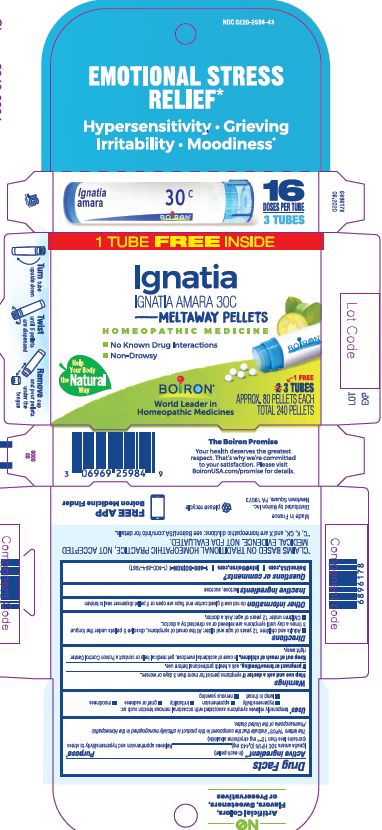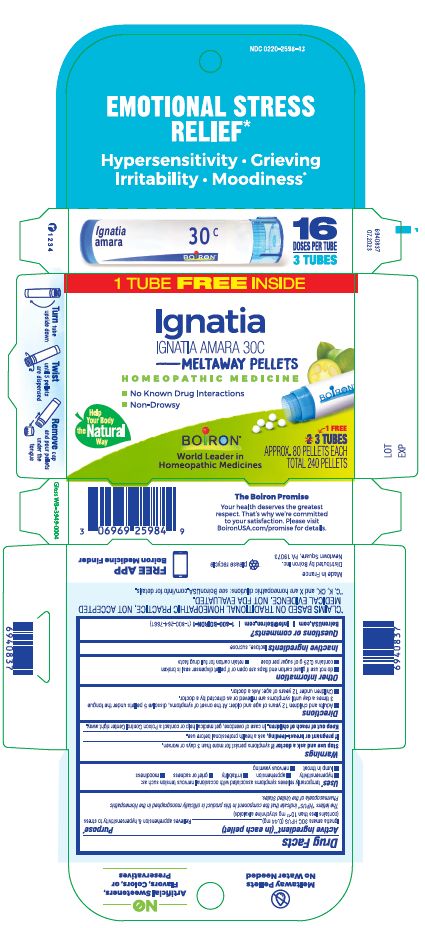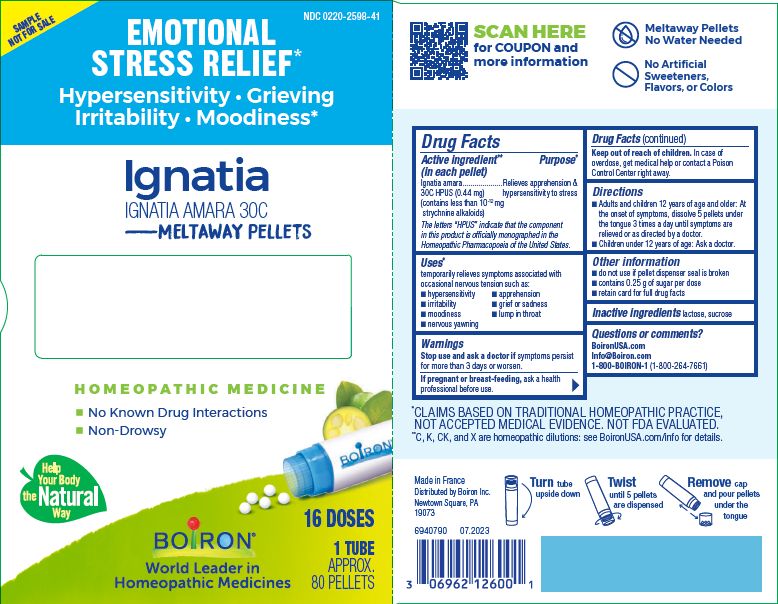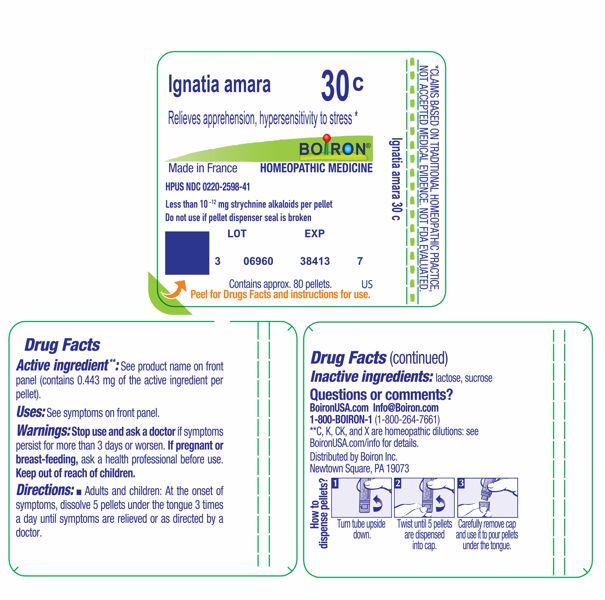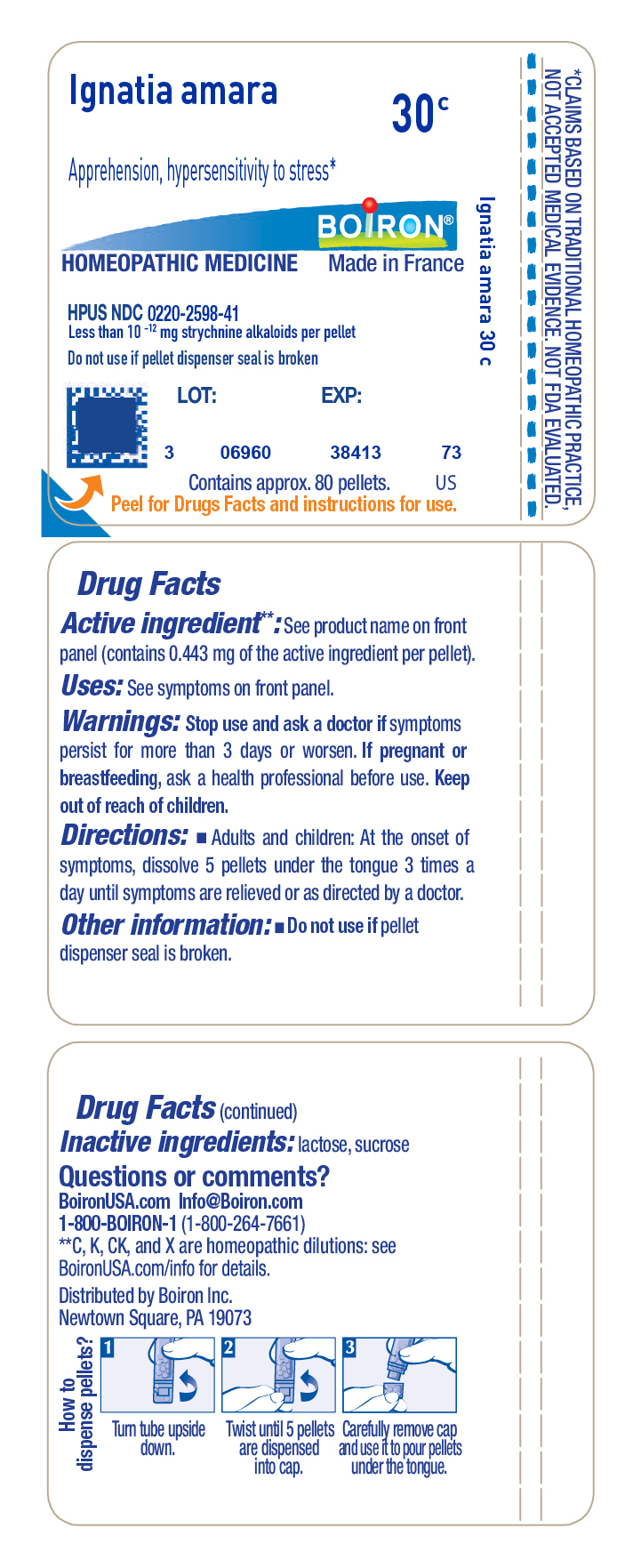 DRUG LABEL: Ignatia amara
NDC: 0220-2598 | Form: PELLET
Manufacturer: Boiron
Category: homeopathic | Type: HUMAN OTC DRUG LABEL
Date: 20251023

ACTIVE INGREDIENTS: STRYCHNOS IGNATII SEED 30 [hp_C]/30 [hp_C]
INACTIVE INGREDIENTS: LACTOSE, UNSPECIFIED FORM; SUCROSE

Ignatia amara 30C

Active ingredient** (in each pellet)

Ignatia amara 30C HPUS (0.44 mg)

Less than 10^-12 mg strychnine alkaloids per pellet

The letters "HPUS" indicate that the components in this product are officially monographed in the Homeopathic Pharmacopoeia of the United States.

PURPOSE

Ignatia amara 30C HPUS .... Relieves apprehension, hypersensitivity to stress

Uses*

temporarily relieves symptoms associated with occasional nervous tension such as:

- hypersensitivity
- apprehension
- irritability
- grief of sadness
- moodiness
- lump in throat
- nervous yawning

Stop use and ask a doctor if symptoms persist for more than 3 days or worsen.

PREGNANCY OR BREAST FEEDING

If pregnant or breast-feeding, ask a health professional before use.

Keep out of reach of children. In case of accidental overdose, get medical help or contact a Poison Control Center right away.

DOSAGE AND ADMINISTRATION

- Adults and children 12 years of age and older: At the onset of symptoms, dissolve 5 pellets under the tongue 3 times a day until symptoms are relieved or as directed by a doctor.
- Children under 12 years of age: Ask a doctor.

INACTIVE INGREDIENT

lactose, sucrose

QUESTIONS

BoironUSA.com Info@boiron.com

1-800-BOIRON-1 (1-800-264-7661)

Made in France

Distributed by Boiron, Inc.

Newtown Square, PA 19073

- do not use if glued carton end flaps are open or if pellet dispenser seal is broken
- contains 0.25 g of sugar per dose
- retain carton for full drug facts

EMOTIONAL STRESS RELIEF*

Hypersensitivity Grieving Irritability Moodiness*

No known drug interactions

1 Tube

3 Tubes

APPROX. 80 PELLETS EACH

TOTAL 240 PELLETS

Turn tube upside down

Twist until 5 pellets are dispensed

Remove cap and pour pellets under the tongue

*CLAIMS BASED ON TRADITIONAL HOMEOPATHIC PRACTICE NOT ACCEPTED MEDICAL EVIDENCE. NOT FDA EVALUATED.

*C,K,CK, and X are homeopathic dilutions: see BoironUSA.com/info for details.